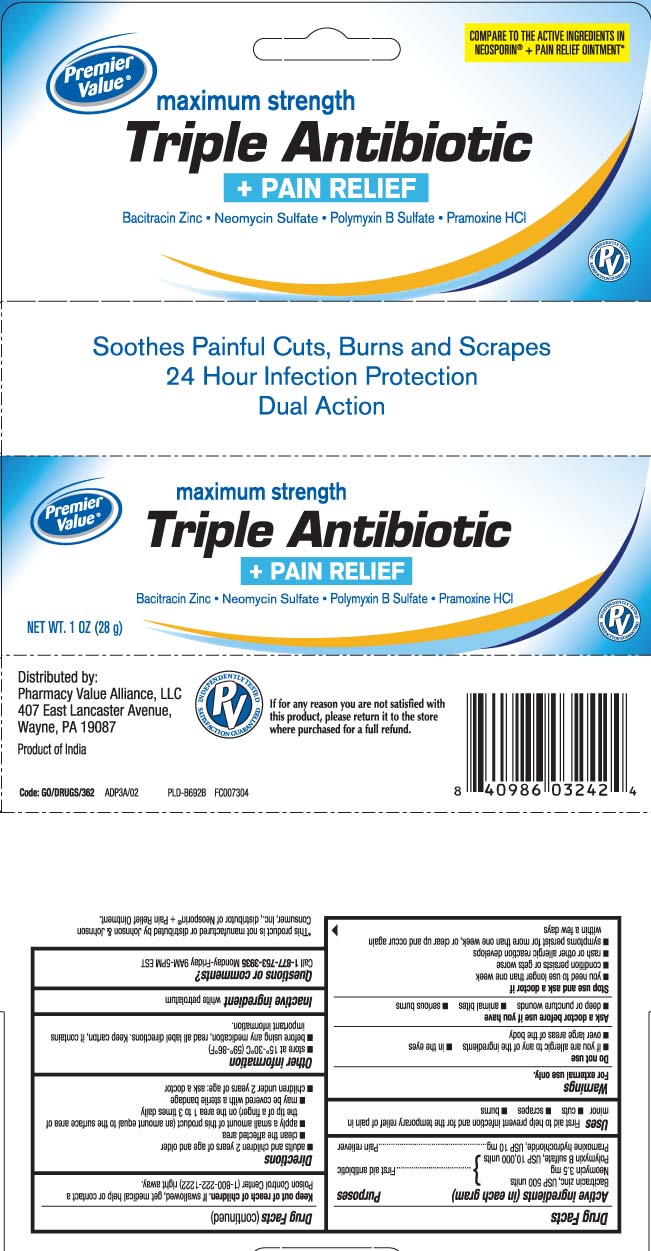 DRUG LABEL: Triple Antibiotic plus Pain Relief
NDC: 68016-715 | Form: OINTMENT
Manufacturer: Chain Drug Consortium, LLC
Category: otc | Type: HUMAN OTC DRUG LABEL
Date: 20250701

ACTIVE INGREDIENTS: BACITRACIN ZINC 500 [USP'U]/1 g; NEOMYCIN SULFATE 3.5 mg/1 g; POLYMYXIN B SULFATE 10000 [USP'U]/1 g; PRAMOXINE HYDROCHLORIDE 10  mg/1 g
INACTIVE INGREDIENTS: PETROLATUM

Triple Antibiotic Plus Pain Relief Maximum Strength Ointment - Premier Value

Active ingredients (in each gram)

Bacitracin zinc, USP 500 units
Neomycin 3.5 mg
Polymyxin B sulfate, USP 10,000 units
Pramoxine hydrochloride, USP 10 mg

Purposes

First aid antibiotic

Pain reliever

Uses

First aid to help prevent infection and for the temporary relief of pain in minor

- cuts
- scrapes
- burns

Warnings

For external use only

Do not use

- if you are allergic to any of the ingredients
- in the eyes
- over large areas of the body

Ask a doctor before use if you have

- deep or puncture wounds
- animal bites
- serious burns

Stop use and ask a doctor if

- you need to use longer than one week
- condition persists or gets worse
- rash or other allergic reaction develops
- symptoms persist for more than one week, or clear up and occur again within a few days

Keep out of reach of children.

If swallowed, get medical help or contact a Poison Control Center (1-800-222-1222) right away.

Directions

- Adults and children 2 years of age and older
  - clean affected area
  - apply a small amount of this product (an amount equal to the surface area of the tip of a finger) on the area 1 to 3 times daily
  - may be covered with a sterile bandage
- Children under 2 years of age: ask a doctor

Other information

- Store at 15°-30°C (59°-86°F)
- Before using any medication, read all label directions. Keep carton, it contains important information.

Inactive ingredient

white petrolatum

Questions or comments?

Call 1-877-753-3935 Monday-Friday 9AM-5PM EST

Principal display panel

COMPARE TO THE ACTIVE INGREDIENTS IN NEOSPORIN® + PAIN RELIEF OINTMENT*

maximum strength

Triple Antibiotic

+ PAIN RELIEF

Bacitracin Zinc • Neomycin Sulfate • Polymyxin B Sulfate • Pramoxine HCl

Soothe Painful Cuts, Burns and Scrapes

24 Hour Infection Protection

Dual Action

*This product is not manufactured or distributed by Johnson & Johnson Consumer, Inc., Distributor of Neosporin® + Pain Relief Ointment.

Distributed by:

Pharmacy Value Alliance, LLC

407 East Lancaster Avenue,

Wayne, PA 19087

Package label

PREMIER VALUE Maximum Strength Triple Antibiotic + Pain Relief